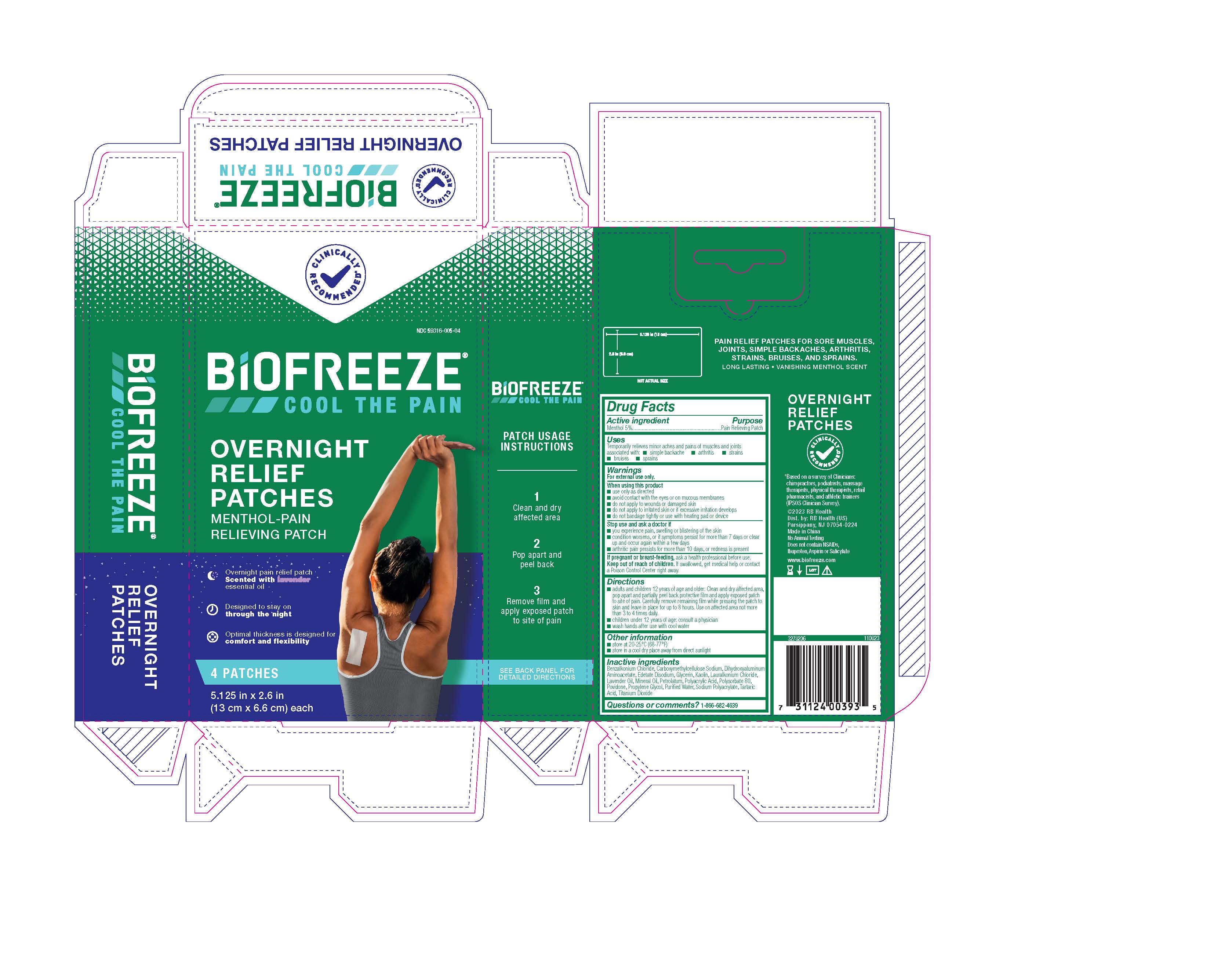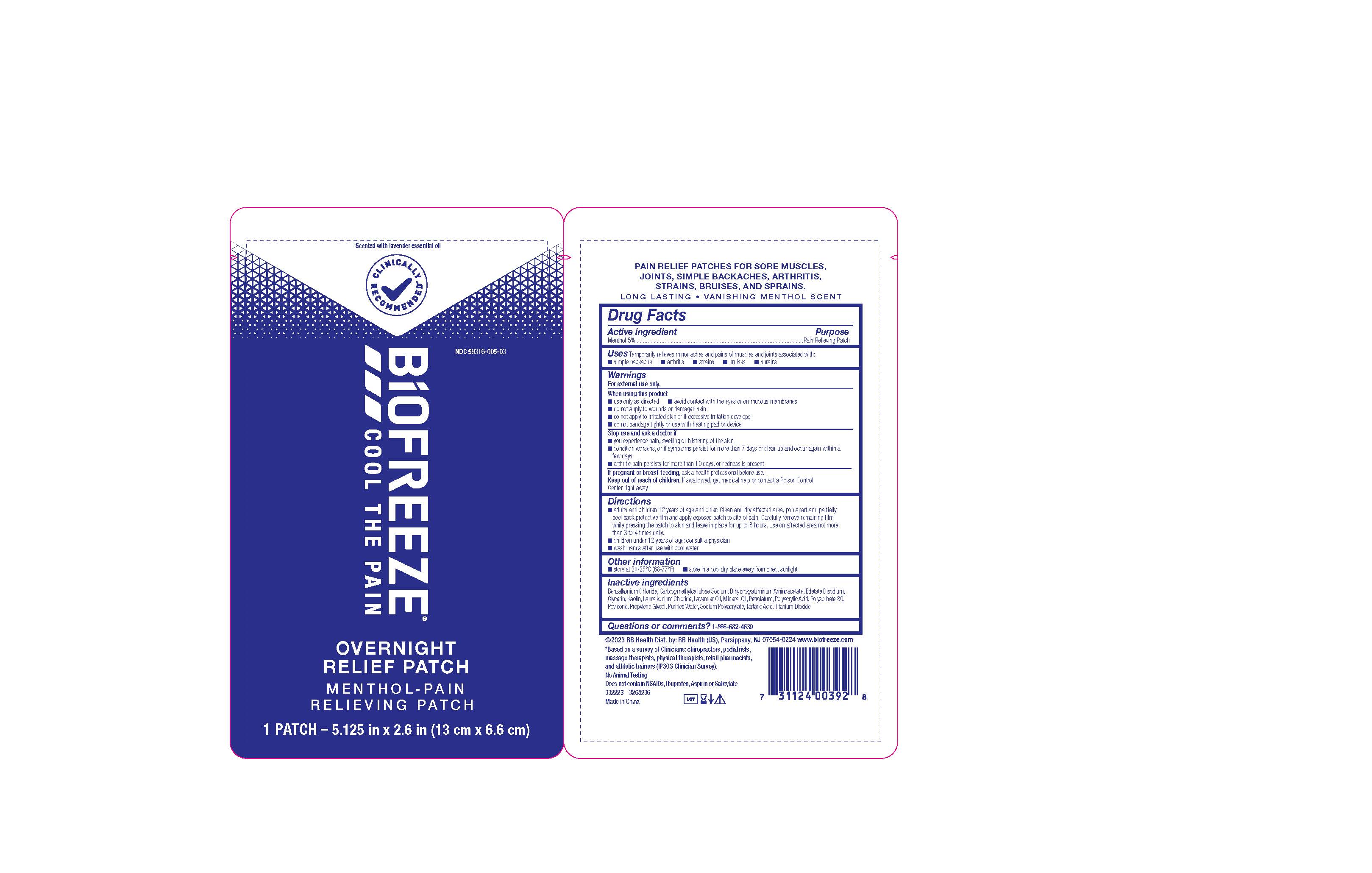 DRUG LABEL: Biofreeze Overnight Relief
NDC: 59316-005 | Form: PATCH
Manufacturer: RB Health (US) LLC
Category: otc | Type: HUMAN OTC DRUG LABEL
Date: 20231213

ACTIVE INGREDIENTS: MENTHOL, UNSPECIFIED FORM 0.3 g/6 g
INACTIVE INGREDIENTS: BENZALKONIUM CHLORIDE; CARBOXYMETHYLCELLULOSE SODIUM, UNSPECIFIED; DIHYDROXYALUMINUM AMINOACETATE; EDETATE DISODIUM; GLYCERIN; KAOLIN; LAURALKONIUM CHLORIDE; LAVENDER OIL; MINERAL OIL; PETROLATUM; POLYSORBATE 80; PROPYLENE GLYCOL; POVIDONE, UNSPECIFIED; TARTARIC ACID; TITANIUM DIOXIDE; WATER; POLYACRYLIC ACID (450000 MW); SODIUM POLYACRYLATE (2500000 MW)

Biofreeze®Overnight Relief Patch

Drug Facts

Active ingredient

Menthol 5%

Purpose

Pain Relieving Patch

Uses

Temporarily relieves minor aches and pains of muscles and joints associated with:

- simple backache
- arthritis
- strains
- bruises
- sprains

Warnings

For external use only.

When using this product

- use only as directed
- avoid contact with the eyes or on mucous membranes
- do not apply to wounds or damaged skin
- do not apply to irritated skin or if excessive irritation develops
- do not bandage tightly or use with heating pad or device

Stop use and ask a doctor if

- you experience pain, swelling or blistering of the skin
- condition worsens, or if symptons persist for more than 7 days or clear up and occur again within a few days
- arthritic pain persists for more than 10 days, or redness is present

PREGNANCY OR BREAST FEEDING

If pregnant or breast-feeding,ask a health professional before use.

Keep out of reach of children.If swallowed, get medical help or contact a Poison Control Center right away.

Directions

- adults and children 12 years of age and older: Clean and dry affected area pop apart and partially peel back protective film and apply exposed patch to site of pain. Carefully remove remaining film while pressing the patch to skin and leave in place for up to 8 hours. Use on affected area not more than 3 to 4 times daily.
- children under 12 years of age: consult a physician
- wash hands after use with cool water

Other information

- store at 20-25° (68-77°F)
- store in a cool dry place away from direct sunlight

Inactive ingredients

Benzalkonium Chloride, Carboxymethylcellulose Sodium, Dihydroxyaluminum Aminoacetate, Edetate Disodium, Glycerin, Kaolin, Lauralkonium Chloride, Lavender Oil, Mineral Oil, Petrolatum, Polyacrylic Acid, Polysorbate 80, Povidone, Propylene Glycol, Purified Water, Sodium Polyacrylate, Tartaric Acid, Titanium Dioxide

Questions or comments?

1-866-682-4639

Dist. by: RB Health (US)
Parsippany, NJ 07054-0224

Made in China

PRINCIPAL DISPLAY PANEL - 4 Patch Pouch Carton

CLINICALLY
RECOMMENDED

NDC 59316-005-04

BIOFREEZE®
COOL THE PAIN

OVERNIGHT
RELIEF
PATCHES

MENTHOL-TOPICAL
ANALGESIC

Overnight pain relief patch
Scented with lavender
essential oil

Designed to stay on
through the night

Optimal thickness is designed for comfort and flexibility

4 PATCHES

5.125 in x 2.6 in
(13 cm x 6.6 cm) each